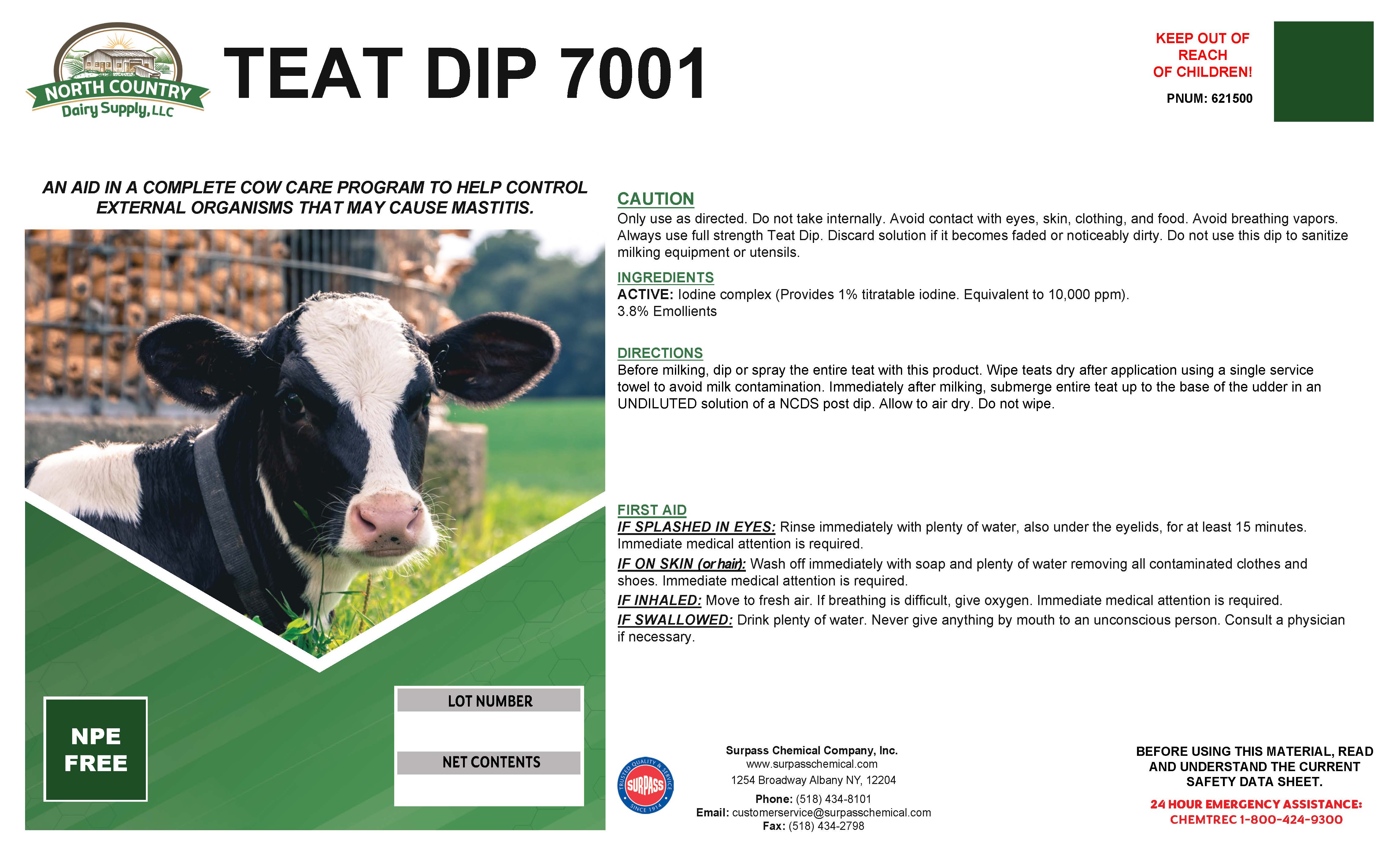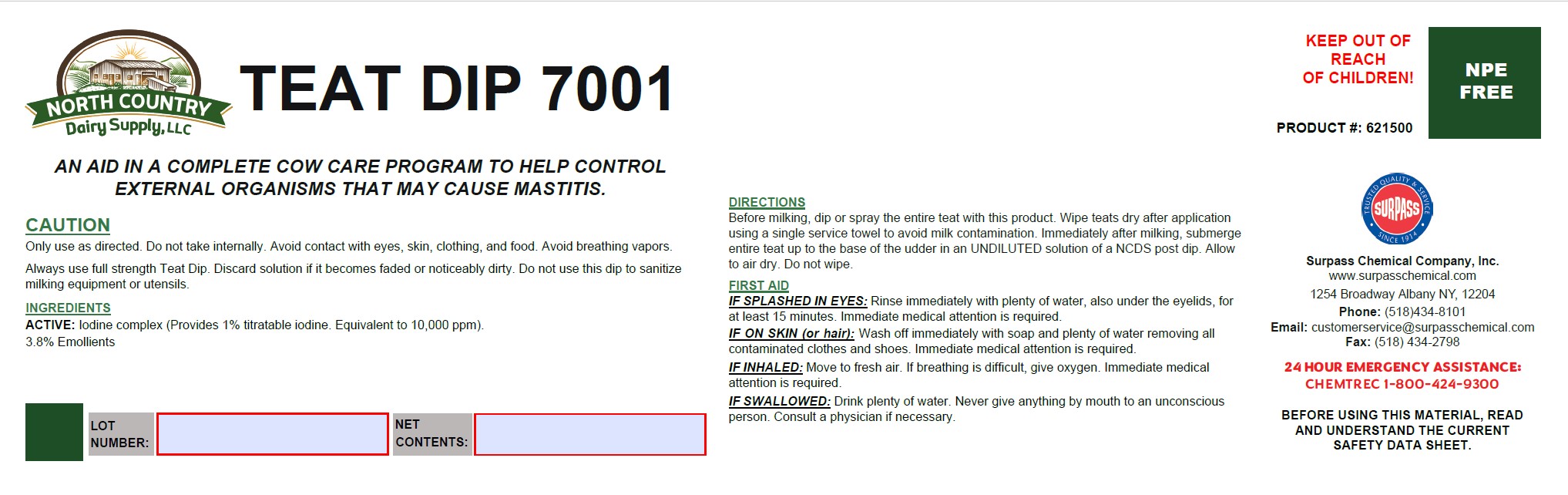 DRUG LABEL: Teat Dip 7001
NDC: 86067-0117 | Form: SOLUTION
Manufacturer: Surpass Chemical Company, Inc.
Category: animal | Type: OTC ANIMAL DRUG LABEL
Date: 20240503

ACTIVE INGREDIENTS: IODINE 0.04724 kg/1 kg
INACTIVE INGREDIENTS: WATER 0.83561 kg/1 kg; C9-11 PARETH-8 0.07 kg/1 kg; GLYCERIN 0.038 kg/1 kg; TRISODIUM CITRATE DIHYDRATE 0.00675 kg/1 kg; Xanthan GUM 0.0008 kg/1 kg; 1,3-BUTYLENE GLYCOL DIOLEATE 0.0016 kg/1 kg

Teat Dip 7001

DESCRIPTION

TEAT DIP 7001

AN AID IN A COMPLETE COW CARE PROGRAM TO HELP CONTROL EXTERNAL ORGANISMS THAT MAY CAUSE MASTITIS. PNUM: 621500

KEEP OUT OF

REACH
OF CHILDREN!

GENERAL PRECAUTIONS

CAUTION

Only use as directed. Do not take internally. Avoid contact with eyes, skin, clothing, and food. Avoid breathing vapors. Always use full strength Teat Dip. Discard solution if it becomes faded or noticeably dirty. Do not use this dip to sanitize milking equipment or utensils.

ACTIVE INGREDIENT

INGREDIENTS

ACTIVE: Iodine complex (Provides 1% titratable iodine. Equivalent to 10,000 ppm).
3.8% Emollients

DIRECTIONS

Before milking, dip or spray the entire teat with this product. Wipe teats dry after application using a single service towel to avoid milk contamination. Immediately after milking, submerge entire teat up to the base of the udder in an UNDILUTED solution of a NCDS post dip. Allow to air dry. Do not wipe.

OTHER SAFETY INFORMATION

FIRST AID:
IF SPLASHED IN EYES: Rinse immediately with plenty of water, also under the eyelids, for at least 15 minutes. Immediate medical attention is required.
IF ON SKIN (or hair): Wash off immediately with soap and plenty of water removing all contaminated clothes and shoes. Immediate medical attention is required.
IF INHALED: Move to fresh air. If breathing is difficult, give oxygen. Immediate medical attention is required.

IF SWALLOWED: Drink plenty of water. Never give anything by mouth to an unconscious person. Consult a physician if necessary.

SAFE HANDLING WARNING

BEFORE USING THIS MATERIAL, READ AND
UNDERSTAND THE CURRENT SAFETY DATA SHEET.

24 HOUR EMERGENCY ASSISTANCE:

CHEMTREC 1-800-424-9300

Surpass Chemical Company, Inc.
www.surpasschemical.com
1254 Broadway Albany NY, 12204

Phone: (518) 434-8101

Email: customerservice@surpasschemical.com

Fax: (518) 434-2798